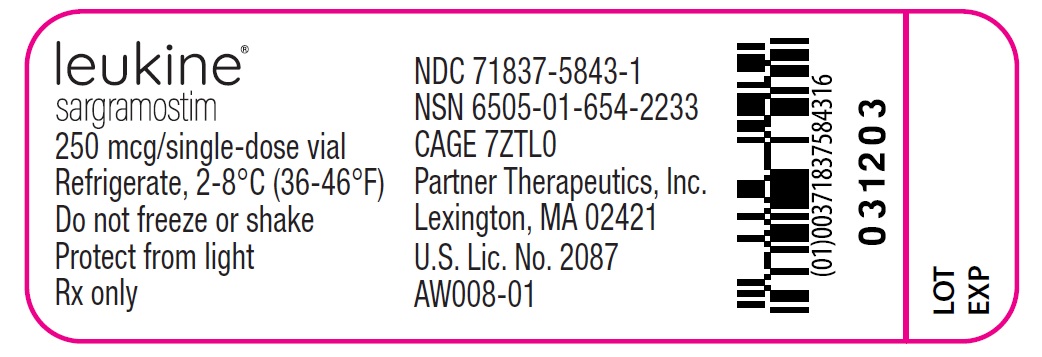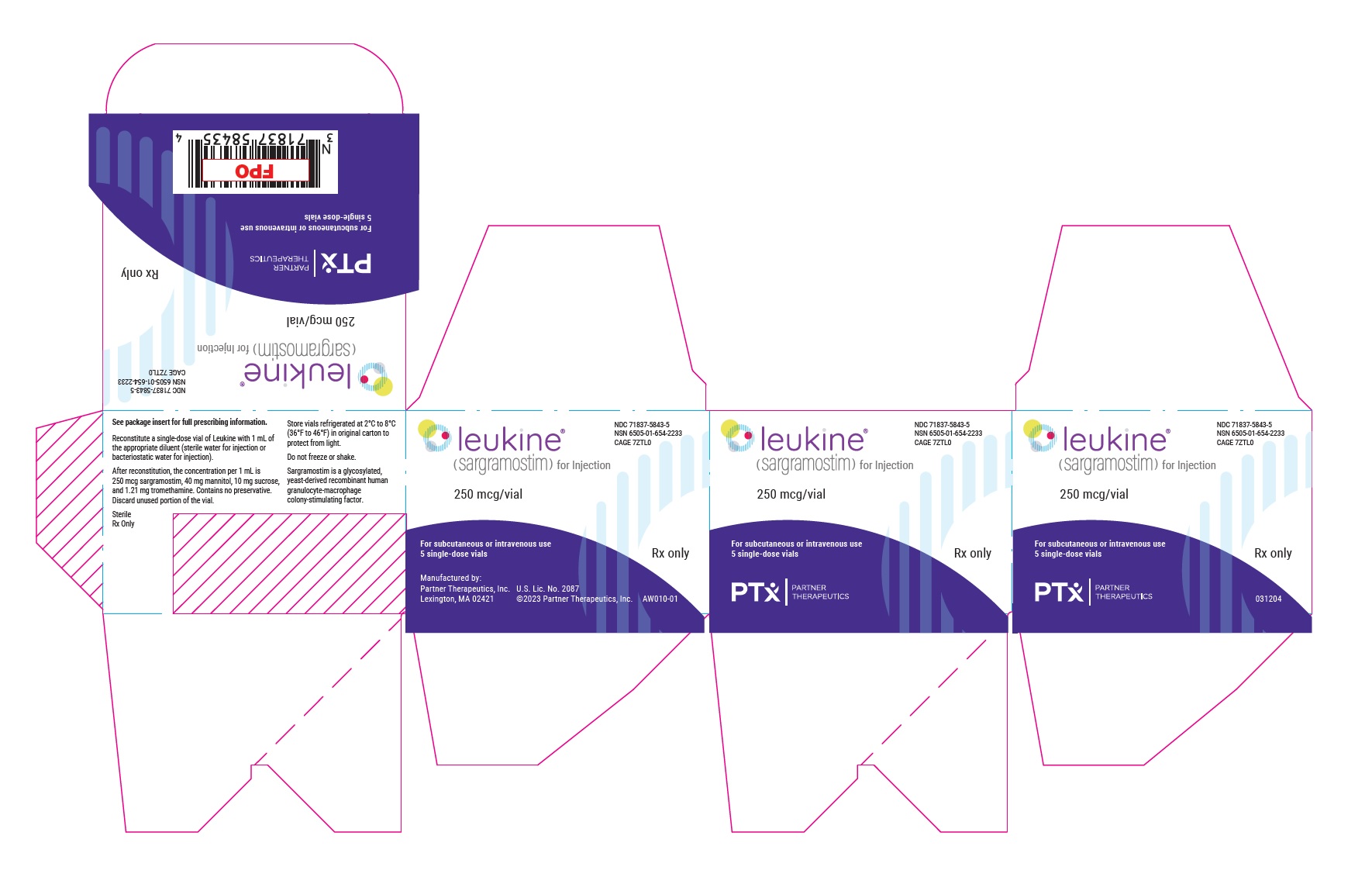 DRUG LABEL: Leukine
NDC: 71837-5843 | Form: INJECTION, POWDER, LYOPHILIZED, FOR SOLUTION
Manufacturer: Partner Therapeutics, Inc.
Category: prescription | Type: HUMAN PRESCRIPTION DRUG LABEL
Date: 20241206

ACTIVE INGREDIENTS: SARGRAMOSTIM 250 ug/1 mL
INACTIVE INGREDIENTS: MANNITOL 40 mg/1 mL; SUCROSE 10 mg/1 mL; TROMETHAMINE 1.2 mg/1 mL; WATER; HYDROCHLORIC ACID

HIGHLIGHTS OF PRESCRIBING INFORMATION

These highlights do not include all the information needed to use LEUKINE safely and effectively. See full prescribing information for LEUKINE.
LEUKINE® (sargramostim) for injection, for subcutaneous or intravenous use
Initial U.S. Approval: 1991

1 INDICATIONS AND USAGE

LEUKINE is a leukocyte growth factor indicated:

- To shorten time to neutrophil recovery and to reduce the incidence of severe and life-threatening infections and infections resulting in death following induction chemotherapy in adult patients 55 years and older with acute myeloid leukemia (AML). (1.1)
- For the mobilization of hematopoietic progenitor cells into peripheral blood for collection by leukapheresis and autologous transplantation in adult patients. (1.2)
- For the acceleration of myeloid reconstitution following autologous bone marrow or peripheral blood progenitor cell transplantation in adult and pediatric patients 2 years of age and older. (1.3)
- For the acceleration of myeloid reconstitution following allogeneic bone marrow transplantation in adult and pediatric patients 2 years of age and older. (1.4)
- For treatment of delayed neutrophil recovery or graft failure after autologous or allogeneic bone marrow transplantation in adult and pediatric patients 2 years of age and older. (1.5)
- To increase survival in adult and pediatric patients from birth to 17 years of age acutely exposed to myelosuppressive doses of radiation (Hematopoietic Syndrome of Acute Radiation Syndrome [H-ARS]). (1.6)

2 DOSAGE AND ADMINISTRATION

See Full Prescribing Information for dosage adjustments and timing of administration (2.1-2.6).

- AML, Neutrophil recovery following chemotherapy:
  - 250 mcg/m^2/day administered intravenously over a 4-hour period. (2.1)
- Mobilization of peripheral blood progenitor cells:
  - 250 mcg/m^2/day administered intravenously over 24 hours or subcutaneous injection once daily. (2.2)
- Post peripheral blood progenitor cell transplantation:
  - 250 mcg/m^2/day administered intravenously over 24 hours or subcutaneous injection once daily. (2.3)
- Myeloid reconstitution after autologous or allogeneic BMT:
  - 250 mcg/m^2/day administered intravenously over a 2-hour period. (2.4)
- BMT failure or engraftment delayed:
  - 250 mcg/m^2/day for 14 days as a 2-hour intravenous infusion. (2.5)
- Patients acutely exposed to myelosuppressive doses of radiation, administer once daily as subcutaneous injection:
  - Adults and pediatric patients weighing >40 kg: 7 mcg/kg
  - Pediatric patients 15 kg to 40 kg: 10 mcg/kg
  - Pediatric patients <15 kg: 12 mcg/kg (2.6)

3 DOSAGE FORMS AND STRENGTHS

- For injection (lyophilized powder): 250 mcg of sargramostim in single-dose vial for reconstitution (3)

4 CONTRAINDICATIONS

- Do not administer LEUKINE to patients with a history of serious allergic reactions, including anaphylaxis, to human granulocyte-macrophage colony stimulating factor such as sargramostim, yeast-derived products, or any component of the product. (4)

5 WARNINGS AND PRECAUTIONS

- Hypersensitivity Reactions: Permanently discontinue LEUKINE in patients with serious allergic reactions. (5.1)
- Infusion Related Reactions: Manage using infusion rate reductions or discontinuations. (5.2)
- Effusions and Capillary Leak Syndrome: Manage with dose-reduction, discontinuation, or diuretics. Monitor body weight and hydration status during therapy. (5.4)
- Supraventricular Arrhythmias: Risk may be increased in patients with history of cardiac arrhythmias. Manage medically and discontinue LEUKINE. (5.5)

6 ADVERSE REACTIONS

The most common adverse reactions (incidence >30%) were (6.1):

- In recipients of autologous BMT: fever, nausea, diarrhea, vomiting, mucous membrane disorder, alopecia, asthenia, malaise, anorexia, rash, gastrointestinal disorder and edema.
- In recipients of allogeneic BMT: diarrhea, fever, nausea, rash, vomiting, stomatitis, anorexia, high glucose, alopecia, abdominal pain, low albumin, headache and hypertension.
- In patients with AML: fever, liver toxicity, skin reactions, infections, metabolic laboratory abnormalities, nausea, diarrhea, genitourinary abnormalities, pulmonary toxicity, vomiting, neurotoxicity, stomatitis, alopecia and weight loss.

To report SUSPECTED ADVERSE REACTIONS, contact Partner Therapeutics, Inc., at 1-888-4RX-LEUKINE or FDA at 1-800-FDA-1088 or www.fda.gov/medwatch.

7 DRUG INTERACTIONS

- Use with caution in patients receiving drugs that may potentiate LEUKINE's myeloproliferative effects, such as lithium and corticosteroids. (7.1)

8 USE IN SPECIFIC POPULATIONS

- Pregnancy: Benzyl alcohol–free formulation recommended. May cause fetal harm. (8.1)
- Pediatrics: In infants, avoid use of benzyl alcohol–containing solutions when feasible. (2.7, 5.9, 8.4)
- Lactation: Advise women not to breastfeed. (8.2)

FULL PRESCRIBING INFORMATION

1 INDICATIONS AND USAGE

1.1 Acute Myeloid Leukemia Following Induction Chemotherapy

LEUKINE is indicated to shorten time to neutrophil recovery and to reduce the incidence of severe, life-threatening, or fatal infections following induction chemotherapy in adult patients 55 years and older with acute myeloid leukemia (AML).

1.2 Autologous Peripheral Blood Progenitor Cell Mobilization and Collection

LEUKINE is indicated in adult patients with cancer undergoing autologous hematopoietic stem cell transplantation for the mobilization of hematopoietic progenitor cells into peripheral blood for collection by leukapheresis.

1.3 Autologous Peripheral Blood Progenitor Cell and Bone Marrow Transplantation

LEUKINE is indicated for the acceleration of myeloid reconstitution following autologous peripheral blood progenitor cell (PBPC) or bone marrow transplantation in adult and pediatric patients 2 years of age and older with non-Hodgkin's lymphoma (NHL), acute lymphoblastic leukemia (ALL) and Hodgkin's lymphoma (HL).

1.4 Allogeneic Bone Marrow Transplantation

LEUKINE is indicated for the acceleration of myeloid reconstitution in adult and pediatric patients 2 years of age and older undergoing allogeneic bone marrow transplantation from HLA-matched related donors.

1.5 Allogeneic or Autologous Bone Marrow Transplantation: Treatment of Delayed Neutrophil Recovery or Graft Failure

LEUKINE is indicated for the treatment of adult and pediatric patients 2 years and older who have undergone allogeneic or autologous bone marrow transplantation in whom neutrophil recovery is delayed or failed.

1.6 Acute Exposure to Myelosuppressive Doses of Radiation (H-ARS)

LEUKINE is indicated to increase survival in adult and pediatric patients from birth to 17 years of age acutely exposed to myelosuppressive doses of radiation (Hematopoietic Syndrome of Acute Radiation Syndrome [H-ARS]).

2 DOSAGE AND ADMINISTRATION

2.1 Neutrophil Recovery Following Induction Chemotherapy for Acute Myeloid Leukemia

The recommended dose is 250 mcg/m^2/day administered intravenously over a 4-hour period starting approximately on day 11 or four days following the completion of induction chemotherapy, if the day 10 bone marrow is hypoplastic with less than 5% blasts. If a second cycle of induction chemotherapy is necessary, administer LEUKINE approximately four days after the completion of chemotherapy if the bone marrow is hypoplastic with less than 5% blasts. Continue LEUKINE until an absolute neutrophil count (ANC) greater than 1500 cells/mm^3 for 3 consecutive days or a maximum of 42 days. Do not administer LEUKINE within 24 hours preceding or following receipt of chemotherapy or radiotherapy [see Warnings and Precautions (5.3)].

Dose Modifications
Obtain a CBC with differential twice per week during LEUKINE therapy and modify the dose for the following:

- Leukemic regrowth: Discontinue LEUKINE immediately
- Grade 3 or 4 adverse reactions: Reduce the dose of LEUKINE by 50% or interrupt dosing until the reaction abates
- ANC greater than 20,000 cells/mm^3: Interrupt LEUKINE treatment or reduce the dose by 50%

2.2 Autologous Peripheral Blood Progenitor Cell Mobilization and Collection

The recommended dose is 250 mcg/m^2/day administered intravenously over 24 hours or subcutaneously once daily. Continue at the same dose through the period of PBPC collection. The optimal schedule for PBPC collection has not been established. In clinical studies, collection of PBPC was usually begun after 5 days of LEUKINE and performed daily until protocol specified targets were achieved [see Clinical Studies (14)].

If WBC greater than 50,000 cells/mm^3, reduce the LEUKINE dose by 50%. Consider other mobilization therapy if adequate numbers of progenitor cells are not collected.

2.3 Autologous Peripheral Blood Progenitor Cell and Bone Marrow Transplantation

Autologous Peripheral Blood Progenitor Cell Transplantation

The recommended dose is 250 mcg/m^2/day administered intravenously over 24 hours or subcutaneously once daily beginning immediately following infusion of progenitor cells and continuing until an ANC greater than 1500 cells/mm^3 for three consecutive days is attained. Do not administer LEUKINE within 24 hours preceding or following receipt of chemotherapy or radiotherapy.

Autologous Bone Marrow Transplantation

The recommended dose is 250 mcg/m^2/day administered intravenously over a 2-hour period beginning two to four hours after bone marrow infusion, and not less than 24 hours after the last dose of chemotherapy or radiotherapy. Do not administer LEUKINE until the post marrow infusion ANC is less than 500 cells/mm^3. Continue LEUKINE until an ANC greater than 1500 cells/mm^3 for three consecutive days is attained. Do not administer LEUKINE within 24 hours preceding or following receipt of chemotherapy or radiotherapy [see Warnings and Precautions (5.3)].

2.4 Allogeneic Bone Marrow Transplantation

The recommended dose is 250 mcg/m^2/day administered intravenously over a 2-hour period beginning two to four hours after bone marrow infusion, and not less than 24 hours after the last dose of chemotherapy or radiotherapy. Do not administer LEUKINE until the post marrow infusion ANC is less than 500 cells/mm^3. Continue LEUKINE until an ANC greater than 1500 cells/mm^3 for three consecutive days is attained. Do not administer LEUKINE within 24 hours preceding or following receipt of chemotherapy or radiotherapy [see Warnings and Precautions (5.3)].

Dose Modifications
Obtain a CBC with differential twice per week during LEUKINE therapy and modify the dose as for the following:

- Disease progression or blast cell appearance: Discontinue LEUKINE immediately
- Grade 3 or 4 adverse reactions: Reduce the dose of LEUKINE by 50% or temporarily discontinue until the reaction abates
- WBC greater than 50,000 cells/mm^3 or ANC greater than 20,000 cells/mm^3: Interrupt LEUKINE treatment or reduce the dose by 50%

2.5 Allogeneic or Autologous Bone Marrow Transplantation: Treatment of Delayed Neutrophil Recovery or Graft Failure

The recommended dose is 250 mcg/m^2/day for 14 days as a 2-hour intravenous infusion. The dose can be repeated after 7 days off therapy if neutrophil recovery has not occurred. If neutrophil recovery still has not occurred, a third course of 500 mcg/m^2/day for 14 days may be tried after another 7 days off therapy. If there is still no improvement, it is unlikely that further dose escalation will be beneficial.

Dose Modifications
Obtain a CBC with differential twice per week during LEUKINE therapy and modify the dose as for the following:

- Disease progression or blast cell appearance: Discontinue LEUKINE immediately
- Grade 3 or 4 adverse reactions: Reduce the dose of LEUKINE by 50% or temporarily discontinue until the reaction abates
- WBC greater than 50,000 cells/mm^3 or ANC greater than 20,000 cells/mm^3: Interrupt LEUKINE treatment or reduce the dose by 50%

2.6 Acute Exposure to Myelosuppressive Doses of Radiation (H-ARS)

For patients with H-ARS, the recommended dose of LEUKINE is a subcutaneous injection administered once daily as follows:

- 7 mcg/kg in adult and pediatric patients weighing greater than 40 kg
- 10 mcg/kg in pediatric patients weighing 15 kg to 40 kg
- 12 mcg/kg in pediatric patients weighing less than 15 kg

Administer LEUKINE as soon as possible after suspected or confirmed exposure to radiation doses greater than 2 gray (Gy).

Estimate a patient’s absorbed radiation dose (i.e., level of radiation exposure) based on information from public health authorities, biodosimetry if available, or clinical findings such as time to onset of vomiting or lymphocyte depletion kinetics.

Obtain a baseline CBC with differential and then serial CBCs approximately every third day until the ANC remains greater than 1,000/mm^3 for three consecutive CBCs. Do not delay administration of LEUKINE if a CBC is not readily available.

Continue administration of LEUKINE until the ANC remains greater than 1,000/mm^3 for three consecutive CBCs or exceeds 10,000/mm3 after a radiation-induced nadir.

2.7 Preparation and Administration of LEUKINE

- Do not administer LEUKINE simultaneously with or within 24 hours preceding cytotoxic chemotherapy or radiotherapy or within 24 hours following chemotherapy [see Warnings and Precautions (5.3)].
- LEUKINE for injection is a sterile, preservative-free lyophilized powder that requires reconstitution with 1 mL Sterile Water for Injection (without preservative), USP, to yield a clear, colorless single-dose solution or 1 mL Bacteriostatic Water for Injection, USP (with 0.9% benzyl alcohol as preservative) to yield a clear, colorless single-dose solution.

Use only LEUKINE for injection (lyophilized powder) reconstituted with Sterile Water for Injection without preservatives when administering LEUKINE to neonates or infants to avoid benzyl alcohol exposure [see Warnings and Precautions (5.9)].

Do NOT use an in-line membrane filter for intravenous infusion of LEUKINE.

- Store reconstituted solution under refrigeration at 2°C to 8°C (36°F to 46°F); DO NOT FREEZE.
- In the absence of compatibility and stability information, do not add other medication to infusion solutions containing LEUKINE. Use only 0.9% Sodium Chloride Injection, USP to prepare intravenous infusion solutions.
- Parenteral drug products should be inspected visually for particulate matter and discoloration prior to administration. If particulate matter is present or the solution is discolored, the vial should not be used.

LEUKINE for Injection Preparation

Reconstitute the lyophilized powder with 1 mL of diluent. Do not mix the contents of vials reconstituted with different diluents together. Reconstitute with either Sterile Water for Injection, USP (without preservative) or Bacteriostatic Water for Injection, USP (0.9% benzyl alcohol) for intravenous or subcutaneous administration. Discard any unused portions.

- When reconstituted with Sterile Water for Injection, USP (without preservative), may store the reconstituted solution refrigerated at 2°C to 8°C and must use within 24 hours following reconstitution.
- When reconstituted with Bacteriostatic Water for Injection, USP (0.9% benzyl alcohol), may store the reconstituted solution refrigerated at 2°C to 8°C and must use within 20 days following reconstitution.

LEUKINE for Intravenous Administration

Dilute reconstituted LEUKINE in 0.9% Sodium Chloride Injection, USP. If the final concentration of LEUKINE is less than 10 mcg/mL, add Albumin (Human) to a final concentration of 0.1% [1 mL 5% Albumin (Human) per 1 mL 0.9% Sodium Chloride Injection, USP] to prevent adsorption of LEUKINE to the drug delivery system. LEUKINE for intravenous administration must be used immediately after dilution with 0.9 % Sodium Chloride Injection, USP.

3 DOSAGE FORMS AND STRENGTHS

- For injection: 250 mcg of sargramostim as a white lyophilized powder in a single-dose vial for reconstitution

4 CONTRAINDICATIONS

Do not administer LEUKINE to patients with a history of serious allergic reactions, including anaphylaxis, to human granulocyte-macrophage colony-stimulating factor such as sargramostim, yeast-derived products, or any component of the product. Anaphylactic reactions have been reported with LEUKINE [see Warnings and Precautions (5.1)].

5 WARNINGS AND PRECAUTIONS

5.1 Hypersensitivity Reactions

Serious hypersensitivity reactions, including anaphylactic reactions, have been reported with LEUKINE. Parenteral administration of LEUKINE should be attended by appropriate precautions in case an allergic or untoward reaction occurs. If any serious allergic or anaphylactic reaction occurs, immediately discontinue LEUKINE therapy and institute medical management. Discontinue LEUKINE permanently for patients with serious allergic reactions.

5.2 Infusion Related Reactions

LEUKINE can cause infusion-related reactions. Infusion-related reactions may be characterized by respiratory distress, hypoxia, flushing, hypotension, syncope, and/or tachycardia following the first administration of LEUKINE in a particular cycle. These signs have resolved with symptomatic treatment and usually do not recur with subsequent doses in the same cycle of treatment.

Observe closely during infusion for symptoms, particularly in patients with pre-existing lung disease. If patients display dyspnea or other acute symptoms, reduce the rate of infusion by 50%. If symptoms persist or worsen despite rate reduction, discontinue the LEUKINE infusion. If patient experiences infusion-related reaction, subsequent intravenous infusions may be administered following the standard dose schedule with careful monitoring.

5.3 Risk of Severe Myelosuppression when LEUKINE Administered within 24 hours of Chemotherapy or Radiotherapy

Due to the potential sensitivity of rapidly dividing hematopoietic progenitor cells, LEUKINE should not be administered simultaneously with or within 24 hours preceding cytotoxic chemotherapy or radiotherapy or within 24 hours following chemotherapy. In one controlled study, patients with small cell lung cancer received LEUKINE and concurrent thoracic radiotherapy and chemotherapy or the identical radiotherapy and chemotherapy without LEUKINE. The patients randomized to LEUKINE had significantly higher incidence of adverse reactions, including higher mortality and a higher incidence of grade 3 and 4 infections and grade 3 and 4 thrombocytopenia.

5.4 Effusions and Capillary Leak Syndrome

Edema, capillary leak syndrome, and pleural and/or pericardial effusion, have been reported in patients after LEUKINE administration. In 156 patients enrolled in placebo-controlled studies using LEUKINE at a dose of 250 mcg/m^2/day by 2-hour IV infusion, the reported incidences of fluid retention (LEUKINE vs. placebo) were as follows: peripheral edema, 11% vs. 7%; pleural effusion, 1% vs. 0%; and pericardial effusion, 4% vs. 1%. Capillary leak syndrome was not observed in this limited number of studies; based on other uncontrolled studies and reports from users of marketed LEUKINE, the incidence is estimated to be less than 1%. In patients with preexisting pleural and pericardial effusions, administration of LEUKINE may aggravate fluid retention; however, fluid retention associated with or worsened by LEUKINE has been reversible after interruption or dose reduction of LEUKINE with or without diuretic therapy. LEUKINE should be used with caution in patients with preexisting fluid retention, pulmonary infiltrates, or congestive heart failure. Body weight and hydration status should be carefully monitored during LEUKINE administration.

5.5 Supraventricular Arrhythmias

Supraventricular arrhythmia has been reported in uncontrolled studies during LEUKINE administration, particularly in patients with a previous history of cardiac arrhythmia. These arrhythmias have been reversible after discontinuation of LEUKINE. Use LEUKINE with caution in patients with preexisting cardiac disease.

5.6 Leukocytosis

White blood cell counts of ≥ 50,000/mm^3 were observed in patients receiving LEUKINE. Monitor complete blood counts (CBC) with differential twice per week. Base the decision whether to reduce the dose or interrupt treatment on the clinical condition of the patient [see Dosage and Administration (2.1, 2.4, 2.5, 2.6)]. Following cessation of LEUKINE therapy, excessive blood counts have returned to normal or baseline levels within 3 to 7 days.

5.7 Potential Effect on Malignant Cells

LEUKINE is a growth factor that primarily stimulates normal myeloid precursors. However, the possibility that LEUKINE can act as a growth factor for any tumor type, particularly myeloid malignancies, cannot be excluded. Because of the possibility of tumor growth potentiation, precaution should be exercised when using this drug in any malignancy with myeloid characteristics.

Discontinue LEUKINE therapy if disease progression is detected during LEUKINE treatment.

5.8 Immunogenicity

Treatment with LEUKINE may induce neutralizing anti-drug antibodies. The incidence of anti-sargramostim neutralizing antibodies may be related to duration of exposure to LEUKINE. In a study of patients with normal neutrophil count and a solid tumor in complete response (an unapproved use) treated with LEUKINE for up to 12 months, 82.9% of 41 evaluable patients developed anti-sargramostim neutralizing antibodies and the myelostimulatory effect of LEUKINE was not sustained by day 155 as assessed by WBC count. Use LEUKINE for the shortest duration required [see Adverse Reactions (6.2)].

5.9 Risk of Serious Adverse Reactions in Infants Due to Benzyl Alcohol Preservative

Serious and fatal adverse reactions including “gasping syndrome” can occur in neonates and low birth weight infants treated with benzyl alcohol-preserved drugs, including LEUKINE for injection reconstituted with Bacteriostatic Water for Injection, USP (0.9% benzyl alcohol). The “gasping syndrome" is characterized by central nervous system depression, metabolic acidosis, and gasping respirations.

Avoid administration of solutions containing benzyl alcohol (including LEUKINE for injection reconstituted with Bacteriostatic Water for Injection, USP [0.9% benzyl alcohol]) to neonates and low birth weight infants. Instead, administer lyophilized LEUKINE reconstituted with Sterile Water for Injection, USP [see Dosage and Administration (2.7)].

If LEUKINE for injection reconstituted with Bacteriostatic Water for Injection, USP (0.9% benzyl alcohol) must be used in neonates and low birth weight infants, consider the combined daily metabolic load of benzyl alcohol from all sources including LEUKINE (LEUKINE for injection reconstituted with Bacteriostatic Water contains 9 mg of benzyl alcohol per mL). The minimum amount of benzyl alcohol at which serious adverse reactions may occur is not known [see Use in Specific Populations (8.4) and Dosage and Administration (2.7)].

6 ADVERSE REACTIONS

The following serious adverse reactions are discussed in greater detail in other sections of the labeling:

- Hypersensitivity Reactions [see Warnings and Precautions (5.1)]
- Infusion Related Reactions [see Warnings and Precautions (5.2)]
- Risk of Severe Myelosuppression when LEUKINE Administered within 24 Hours of Chemotherapy or Radiotherapy [see Warnings and Precautions (5.3)]
- Effusions and Capillary Leak Syndrome [see Warnings and Precautions (5.4)]
- Supraventricular Arrhythmias [see Warnings and Precautions (5.5)]
- Leukocytosis [see Warnings and Precautions (5.6)]
- Potential Effect on Malignant Cells [see Warnings and Precautions (5.7)]
- Immunogenicity [see Warnings and Precautions (5.8)]
- Risk of Serious Adverse Reactions in Infants Due to Benzyl Alcohol Preservative [see Warnings and Precautions (5.9)]

6.1 Clinical Trials Experience

Because clinical trials are conducted under widely varying conditions, adverse reaction rates observed in the clinical trials of a drug cannot be directly compared with rates in the clinical trials of another drug and may not reflect the rates observed in clinical practice.

Autologous Peripheral Blood Progenitor Cell (PBPC) and Bone Marrow Transplantation

Studies 301, 302 and 303 enrolled a total of 156 patients after autologous or allogeneic marrow or PBPC transplantation. In these placebo-controlled studies, pediatric and adult patients received once-daily intravenous infusions of LEUKINE 250 mcg/m^2 or placebo for 21 days.

In Studies 301, 302, and 303, there was no difference in relapse rate between the LEUKINE and placebo-treated patients. Adverse reactions reported in at least 10% of patients who received intravenous LEUKINE or at a rate that was at least 5% higher than the placebo arm are shown in Table 1.

Table 1: Adverse Reactions after Autologous Marrow or PBPC Transplantation in at Least 10% of Patients Receiving Intravenous LEUKINE or at Least 5% Higher than the Placebo Arm
Adverse Reactions by Body System | LEUKINE (n=79) % | Placebo (n=77) % | Adverse Reactions by Body System | LEUKINE (n=79) % | Placebo (n=77) %
Body, General |  |  | Metabolic, Nutritional Disorder
Fever | 95 | 96 | Edema | 34 | 35
Mucous membrane disorder | 75 | 78 | Peripheral edema | 11 | 7
Asthenia | 66 | 51 | Respiratory System
Malaise | 57 | 51 | Dyspnea | 28 | 31
Sepsis | 11 | 14 | Lung disorder | 20 | 23
Digestive System |  |  | Blood and Lymphatic System
Nausea | 90 | 96 | Blood dyscrasia | 25 | 27
Diarrhea | 89 | 82 | Cardiovascular Vascular System
Vomiting | 85 | 90 | Hemorrhage | 23 | 30
Anorexia | 54 | 58 | Urogenital System
GI disorder | 37 | 47 | Urinary tract disorder | 14 | 13
GI hemorrhage | 27 | 33 | Nervous System
Stomatitis | 24 | 29 | CNS disorder | 11 | 16
Liver damage | 13 | 14
Skin and Appendages
Alopecia | 73 | 74
Rash | 44 | 38

Additional Clinically Significant Adverse Reactions Occurring in Less than 10% Incidence

Investigations: Elevated creatinine, elevated bilirubin, elevate transaminases

Allogeneic Bone Marrow Transplantation

In the placebo-controlled trial of 109 patients after allogeneic BMT (Study 9002), acute graft-vs-host disease occurred in 55% on the LEUKINE arm and in 59% on the placebo arm. Adverse reactions reported in at least 10% of patients who received IV LEUKINE or at a rate at least 5% higher than the placebo arm are shown in Table 2.

Table 2: Adverse Reactions after Allogeneic Marrow Transplantation in at Least 10% of Patients Receiving Intravenous LEUKINE or at Least 5% Higher than the Placebo Arm
Adverse Reactions by Body System | LEUKINE (n=53) % | Placebo (n=56) % | Adverse Reactions by Body System | LEUKINE (n=53) % | Placebo (n=56) %
Body, General |  |  | Eye hemorrhage | 11 | 0
Fever | 77 | 80 | Cardiovascular Vascular System
Abdominal pain | 38 | 23 | Hypertension | 34 | 32
Headache | 36 | 36 | Tachycardia | 11 | 9
Chills | 25 | 20 | Metabolic / Nutritional Disorders
Pain | 17 | 36 | Bilirubinemia | 30 | 27
Asthenia | 17 | 20 | Hyperglycemia | 25 | 23
Chest pain | 15 | 9 | Peripheral edema | 15 | 21
Digestive System |  |  | Increased creatinine | 15 | 14
Diarrhea | 81 | 66 | Hypomagnesemia | 15 | 9
Nausea | 70 | 66 | Increased SGPT | 13 | 11
Vomiting | 70 | 57 | Edema | 13 | 11
Stomatitis | 62 | 63 | Respiratory System
Anorexia | 51 | 57 | Pharyngitis | 23 | 13
Dyspepsia | 17 | 20 | Epistaxis | 17 | 16
Hematemesis | 13 | 7 | Dyspnea | 15 | 14
Dysphagia | 11 | 7 | Rhinitis | 11 | 14
GI hemorrhage | 11 | 5 | Blood and Lymphatic System
Skin and Appendages |  |  | Thrombocytopenia | 19 | 34
Rash | 70 | 73 | Leukopenia | 17 | 29
Alopecia | 45 | 45 | Nervous System
Pruritus | 23 | 13 | Paresthesia | 11 | 13
Musculoskeletal System |  |  | Insomnia | 11 | 9
Bone pain | 21 | 5 | Anxiety | 11 | 2
Arthralgia | 11 | 4 | Laboratory Abnormalities*
Special Senses |  |  | High glucose | 49 | 41
 |  |  | Low albumin | 36 | 27
 |  |  | High BUN | 17 | 23
* Grade 3 and 4 laboratory abnormalities only. Denominators may vary due to missing laboratory measures.

Acute Myeloid Leukemia Following Induction Chemotherapy

Nearly all patients in both arms developed leukopenia, thrombocytopenia, and anemia. Adverse reactions reported in at least 10% of patients who received LEUKINE or at least 5% higher than the placebo arm are reported in Table 3.

Table 3: Adverse Reactions after Treatment of AML in at Least 10% of Patients Receiving Intravenous LEUKINE or at Least 5% Higher than the Placebo Arm
Adverse Reactions by Body System | LEUKINE (n=52) % | Placebo (n=47) % | Adverse Reactions by Body System | LEUKINE (n=52) % | Placebo (n=47) %
Body, General |  |  | Metabolic, Nutritional Disorder
Fever (no infection) | 81 | 74 | Metabolic Laboratory Abnormalities | 58 | 49
Infection | 65 | 68 | Edema | 25 | 23
Weight loss | 37 | 28 | Respiratory System
Chills | 19 | 26 | Pulmonary toxicity | 48 | 64
Allergy | 12 | 15 | Blood and Lymphatic System
Digestive System |  |  | Coagulation | 19 | 21
Nausea | 58 | 55 | Cardiovascular System
Liver toxicity | 77 | 83 | Hemorrhage | 29 | 43
Diarrhea | 52 | 3 | Hypertension | 25 | 32
Vomiting | 46 | 34 | Cardiac | 23 | 32
Stomatitis | 42 | 43 | Hypotension | 13 | 26
Anorexia | 13 | 11 | Urogenital System
Skin and Appendages |  |  | GU abnormalities | 50 | 57
Skin Reactions | 77 | 45 | Nervous System
Alopecia | 37 | 51 | Neuro-clinical | 42 | 53
 |  |  | Neuro-motor | 25 | 26
 |  |  | Neuro-psych | 15 | 26

There was no significant difference between the arms in the proportion of patients achieving complete remission (CR; 69% in the LEUKINE group and 55% in the placebo group). There was also no significant difference in relapse rates; 12 of 36 patients who received LEUKINE and five of 26 patients who received placebo relapsed within 180 days of documented CR (p=0.26). The study was not sized to assess the impact of LEUKINE treatment on response.

Graft Failure

In a historically controlled study of 86 patients with AML, the LEUKINE treated group exhibited an increased incidence of weight gain (p=0.007), low serum proteins, and prolonged prothrombin time (p=0.02) when compared to the control group. Two LEUKINE treated patients had progressive increase in circulating monocytes and promonocytes and blasts in the marrow, which reversed when LEUKINE was discontinued. The historical control group exhibited an increased incidence of cardiac events (p=0.018), liver function abnormalities (p=0.008), and neurocortical hemorrhagic events (p=0.025). Headache (26%), pericardial effusion (25%), arthralgia (21%), and myalgia (18%) were also reported in patients treated with LEUKINE in the graft failure study.

6.2 Immunogenicity

As with all therapeutic proteins, there is the potential for immunogenicity with LEUKINE. The detection of antibody formation is highly dependent on the sensitivity and specificity of the assay. Additionally, the observed incidence of antibody positivity in an assay may be influenced by several factors, including assay methodology, sample handling, timing of sample collection, duration of treatment, concomitant medications, and underlying disease. For these reasons, comparison of the incidence of antibodies to sargramostim in the studies described below with the incidence of antibodies in other studies or other products may be misleading.

In 214 patients with a variety of underlying diseases, neutralizing anti-sargramostim antibodies were detected in 5 patients (2.3%) after receiving LEUKINE by continuous IV infusion (3 patients) or SC injection (2 patients) for 28 to 84 days in multiple courses (as assessed by GM-CSF dependent human cell-line proliferation assay). All 5 patients had impaired hematopoiesis before the administration of LEUKINE, and consequently the effect of the development of anti-sargramostim antibodies on normal hematopoiesis could not be assessed.

Antibody studies of 75 patients with Crohn's disease (a disease for which LEUKINE is not indicated), with normal hematopoiesis and no other immunosuppressive drugs, receiving LEUKINE daily for 8 weeks by SC injection, showed 1 patient (1.3%) with detectable neutralizing anti-sargramostim antibodies (as assessed by GM-CSF dependent human cell-line proliferation assay).

In an experimental use trial where LEUKINE was given for an extended period, 53 patients with melanoma in complete remission (a disease for which LEUKINE is not indicated) received adjuvant therapy with LEUKINE 125 mcg/m^2 once daily (maximum dose 250 mcg) from day 1 to 14 every 28 days for 1 year. Serum samples from patients assessed at day 0, 2 weeks, 1 month, and 5 and/or 12 months were tested retrospectively for the presence of anti-sargramostim antibodies. Of 43 evaluable patients (having at least 3 timepoint samples post treatment), 42 (97.7%) developed anti-sargramostim binding antibody as assessed by ELISA and confirmed using an immunoprecipitation assay. Of these 42 patients, 41 had sufficient sample and were further tested: 34 patients (82.9%) developed anti-sargramostim neutralizing antibodies (as determined by a cell based luciferase reporter gene neutralizing antibody assay); 17 (50%) of these patients did not have a sustained pharmacodynamic effect of LEUKINE by day 155 as assessed by WBC counts. This study provided limited assessment of the impact of antibody formation on the safety and efficacy of LEUKINE.

Serious allergic and anaphylactoid reactions have been reported with LEUKINE, but the rate of occurrence of antibodies in such patients has not been assessed.

6.3 Postmarketing Experience

The following adverse reactions have been identified during postapproval use of LEUKINE in clinical trials and/or postmarketing surveillance. Because these reactions are reported voluntarily from a population of uncertain size, it is not always possible to reliably estimate their frequency or establish a causal relationship to drug exposure.

- Infusion related reactions including dyspnea, hypoxia, flushing, hypotension, syncope and/or tachycardia [see Warnings and Precautions [see Warnings and Precautions (5.1)]
- Serious allergic reactions/hypersensitivity, including anaphylaxis, skin rash, urticaria, generalized erythema, and flushing [see Warnings and Precautions (5.2)]
- Effusions and capillary leak syndrome [see Warnings and Precautions (5.3)]
- Supraventricular arrhythmias [see Warnings and Precautions (5.4)]
- Leukocytosis including eosinophilia [see Warnings and Precautions (5.6)]
- Thromboembolic events
- Pain, including chest, abdominal, back, and joint pain
- Injection site reactions

7 DRUG INTERACTIONS

7.1 Concomitant Use with Products that Induce Myeloproliferation

Avoid the concomitant use of LEUKINE and products that induce myeloproliferation (such as lithium and corticosteroids). Such products may increase the myeloproliferative effects of LEUKINE. Monitor patients receiving both LEUKINE and products that induce myeloproliferation frequently for clinical and laboratory signs of excess myeloproliferative effects.

8 USE IN SPECIFIC POPULATIONS

8.1 Pregnancy

Risk Summary

LEUKINE for injection reconstituted with Bacteriostatic Water for Injection, USP contain 0.9% benzyl alcohol, which has been associated with gasping syndrome in neonates and infants. The preservative benzyl alcohol can cause serious adverse reactions and death when administered intravenously to neonates and infants. If LEUKINE is needed during pregnancy, reconstitute LEUKINE for injection only with Sterile Water for injection without preservatives [see Dosage and Administration (2.7) and Use in Specific Populations (8.4)].

The limited available data on LEUKINE use in pregnant women are insufficient to inform the drug-associated risk of adverse developmental outcomes. Based on animal studies LEUKINE may cause embryofetal harm. In animal reproduction studies, administration of LEUKINE to pregnant rabbits during organogenesis resulted in adverse developmental outcomes including increased spontaneous abortion at systemic exposures ≥1.3 times the human exposure expected at the recommended human dose [see Data]. Advise pregnant women of the potential risk to a fetus.

The estimated background risk of major birth defects and miscarriage for the indicated population is unknown. All pregnancies have a background risk of birth defect, loss, or other adverse outcomes. In the U.S. general population, the estimated background risks of major birth defects and miscarriage in clinically recognized pregnancies are 2%-4% and 15%-20%, respectively.

Data

Animal data

In an embryofetal developmental study and a prenatal and postnatal study, pregnant rabbits were administered SC doses of LEUKINE during the period of gestation day (GD) 6 to GD19, GD19 to GD28, or GD19 to parturition at 25, 70, and 200 mcg/kg/day. An increase in spontaneous abortions, late resorptions, and post implantation loss, and a reduction in viable fetuses, mean live litter size, and offspring body weight were evident in rabbits treated with LEUKINE at 200 mcg/kg/day. No adverse effects were observed at ≤70 mcg/kg/day.

After the first administration in rabbits, the dose of 200 mcg/kg/day corresponds to a systemic exposure (AUC) of approximately 11-25.3 times the exposures observed in patients treated with the clinical LEUKINE dose of 250 mcg/m^2; however, due to the production of anti-LEUKINE antibodies with repeat administration, the AUC in rabbits was reduced to 1.3-5.5 times the clinical exposure by the end of the dosing periods.

Similarly, after the first administration in rabbits, the dose of 70 mcg/kg/day corresponds to a systemic exposure (AUC) of approximately 7 to 11 times the exposures observed in patients treated with the clinical LEUKINE dose of 250 mcg/m^2; however, due to the production of anti-LEUKINE antibodies with repeat administration, the AUC in rabbits was reduced to 1.0-1.2 times the clinical exposure by the end of the dosing periods.

8.2 Lactation

Risk Summary

There is no information regarding the presence of LEUKINE in human milk, the effects on the breastfed child, or the effects on milk production. Administration of LEUKINE to rabbits during lactation resulted in reduction in postnatal offspring survival [see Data]. Because of the potential for serious adverse reactions advise a lactating woman not to breastfeed during treatment and for at least 2 weeks after the last dose.

Data

There are no data regarding the presence of LEUKINE in rabbit milk. However, in the prenatal and postnatal study, lactating rabbits were administered SC doses of LEUKINE during the period of lactation day (LD) 1 to LD14 at 25, 70, and 200 mcg/kg/day. At doses ≥25 mcg/kg/day a reduction in postnatal offspring survival was observed. Maternal toxicity was also observed at LEUKINE doses ≥25 mcg/kg/day.

After the first administration in rabbits, the dose of 25 mcg/kg/day corresponds to a systemic AUC of approximately 2.6 times the exposure observed in patients treated with the clinical LEUKINE dose of 250 mcg/m^2 however, due to the production of anti-LEUKINE antibodies with repeat administration, the exposure in rabbits decreased to 0.2 times the clinical exposure by the end of the dosing period.

8.4 Pediatric Use

The safety and effectiveness of LEUKINE have been established in pediatric patients 2 years of age and older for autologous peripheral blood progenitor cells and bone marrow transplantation, allogeneic bone marrow transplantation, and treatment of delayed neutrophil recovery or graft failure. Use of LEUKINE for these indications in this age group is based on adequate and well-controlled studies of LEUKINE in adults, in addition to clinical data in 12, 23, and 37 pediatric patients, respectively [See Clinical Studies (14.3, 14.4 and 14.5)]. The pediatric adverse reactions were consistent with those reported in the adult population.

The safety and effectiveness of LEUKINE for pediatric patients less than 2 years of age for autologous peripheral blood progenitor cells and bone marrow transplantation, allogeneic bone marrow transplantation, and treatment of delayed neutrophil recovery or graft failure have not been established.

The use of LEUKINE to increase survival in pediatric patients acutely exposed to myelosuppressive doses of radiation (H-ARS) is based on efficacy studies conducted in animals and clinical data supporting the use of LEUKINE in patients undergoing autologous or allogeneic BMT following myelosuppressive chemotherapy with or without total body irradiation. Efficacy studies of LEUKINE could not be conducted in humans with acute radiation syndrome for ethical and feasibility reasons. Modeling and simulation were used to derive dosing regimens that are predicted to provide pediatric patients with exposure comparable to the observed exposure in adults receiving 7 mcg/kg [see Clinical Pharmacology (12.3)]. The dose for pediatric patients is based on weight [see Dosage and Administration (2.2)].

Safety and effectiveness in pediatric patients have not been established in:

- Acute Myeloid Leukemia: Neutrophil Recovery Following Induction Chemotherapy
- Autologous Peripheral Blood Progenitor Cell Mobilization and Collection

Avoid administration of solutions containing benzyl alcohol [LEUKINE for injection reconstituted with Bacteriostatic Water for Injection, USP (0.9% benzyl alcohol)] to neonates and low birth weight infants. Instead, administer lyophilized LEUKINE reconstituted with Sterile Water for Injection, USP [see Dosage and Administration (2.7)].

Serious adverse reactions including fatal reactions and the “gasping syndrome” occurred in premature infants in the neonatal intensive care unit who received drugs containing benzyl alcohol as a preservative. In these cases, benzyl alcohol dosages of 99 to 234 mg/kg/day produced high levels of benzyl alcohol and its metabolites in the blood and urine (blood levels of benzyl alcohol were 0.61 to 1.38 mmol/L). Additional adverse reactions included gradual neurological deterioration, seizures, intracranial hemorrhage, hematologic abnormalities, skin breakdown, hepatic and renal failure, hypotension, bradycardia, and cardiovascular collapse. Preterm, low birth weight infants may be more likely to develop these reactions because they may be less able to metabolize benzyl alcohol.

If LEUKINE for injection reconstituted with Bacteriostatic Water for Injection, USP (0.9% benzyl alcohol) must be used in neonates and low birth weight infants, consider the combined daily metabolic load of benzyl alcohol from all sources including LEUKINE (LEUKINE for injection reconstituted with Bacteriostatic Water for Injection, USP [0.9% benzyl alcohol] contains 9 mg of benzyl alcohol per mL). The minimum amount of benzyl alcohol at which serious adverse reactions may occur is not known [see Dosage and Administration (2.7)].

8.5 Geriatric Use

Clinical studies of LEUKINE did not include a sufficient numbers of subject aged 65 and over to determine whether they respond differently from younger subjects. Other reported clinical experience has not identified differences in responses between the elderly and younger patients.

10 OVERDOSAGE

Doses up to 100 mcg/kg/day (4,000 mcg/m^2/day or 16 times the recommended dose) were administered to four patients in a Phase 1 uncontrolled clinical study by continuous IV infusion for 7 to 18 days. Increases in WBC up to 200,000 cells/mm^3 were observed. Adverse events reported were dyspnea, malaise, nausea, fever, rash, sinus tachycardia, headache, and chills. All these events were reversible after discontinuation of LEUKINE.

In case of overdosage, discontinue LEUKINE therapy and monitor the patient for WBC increase and respiratory symptoms.

11 DESCRIPTION

Sargramostim is a glycosylated recombinant human granulocyte-macrophage colony-stimulating factor (rhu GM-CSF) produced by recombinant DNA technology in a yeast (S. cerevisiae) expression system. Sargramostim is a glycoprotein of 127 amino acids characterized by three primary molecular species having molecular masses of 19,500, 16,800 and 15,500 Daltons.

The amino acid sequence of sargramostim differs from the natural human GM-CSF by a substitution of leucine at position 23, and the carbohydrate moiety may be different from the native protein. Sargramostim differs from human GM-CSF by one amino acid at position 23, where leucine is substituted for arginine.

LEUKINE (sargramostim) for injection is supplied as a sterile, preservative-free, white lyophilized powder in a single-dose vial for subcutaneous or intravenous use. Reconstitute each single-dose vial with 1 mL of diluent (i.e., sterile water for injection or bacteriostatic water for injection). After reconstitution each single-dose vial contains 250 mcg/mL sargramostim and the inactive ingredients mannitol (40 mg), sucrose (10 mg), and tromethamine (1.21 mg) per mL with a pH range of 7.1 - 7.7 with a deliverable volume of 1 mL (250 mcg).

12 CLINICAL PHARMACOLOGY

12.1 Mechanism of Action

Sargramostim (GM-CSF) belongs to a group of growth factors termed colony-stimulating factors which support survival, clonal expansion, and differentiation of hematopoietic progenitor cells. GM-CSF induces partially committed progenitor cells to divide and differentiate in the granulocyte-macrophage pathways which include neutrophils, monocytes/macrophages and myeloid-derived dendritic cells.

GM-CSF is also capable of activating mature granulocytes and macrophages. GM-CSF is a multilineage factor and, in addition to dose-dependent effects on the myelomonocytic lineage, can promote the proliferation of megakaryocytic and erythroid progenitors. However, other factors are required to induce complete maturation in these two lineages. The various cellular responses (i.e., division, maturation, activation) are induced through GM-CSF binding to specific receptors expressed on the cell surface of target cells.

The biological activity of GM-CSF is species-specific. Consequently, in vitro studies have been performed on human cells to characterize the pharmacological activity of GM-CSF. In vitro exposure of human bone marrow cells to GM-CSF at concentrations ranging from 1-100 ng/mL results in the proliferation of hematopoietic progenitors and in the formation of pure granulocyte, pure macrophage, and mixed granulocyte macrophage colonies. Chemotactic, anti-fungal, and anti-parasitic activities of granulocytes and monocytes are increased by exposure to GM-CSF in vitro. GM-CSF increases the cytotoxicity of monocytes toward certain neoplastic cell lines and activates polymorphonuclear neutrophils to inhibit the growth of tumor cells.

12.2 Pharmacodynamics

LEUKINE stimulates hematopoietic precursor cells and increases neutrophil, eosinophil, megakaryocyte, macrophage, and dendritic cell production. In AML adult patients undergoing induction chemotherapy [see Clinical Studies (14.1)], LEUKINE at daily doses of 250 mcg/m^2 significantly shortened the median duration of ANC <500/mm^3 by 4 days and <1000/mm^3 by 7 days following induction; 75% of patients receiving sargramostim achieved ANC greater than 500/mm^3 by day 16 compared to day 25 for patients receiving placebo. Animal data and clinical data in humans suggest a correlation between sargramostim exposure and the duration of severe neutropenia as a predictor of efficacy. At doses of 250 mcg/m^2(approximately 7 mcg/kg in a 70 kg human with a body surface area of 1.96), daily LEUKINE treatment reduced the duration of severe neutropenia.

12.3 Pharmacokinetics

Intravenous Administration (IV)

Peak concentrations of sargramostim were observed in blood samples obtained during or immediately after completion of LEUKINE infusion.

Subcutaneous Administration (SC)

Based on a population pharmacokinetics analysis of lyophilized LEUKINE data, the mean Cmax after a 7 mcg/kg SC dose (equivalent to a 250 mcg/m^2 dose in a 70 kg human with a body surface area of 1.96) was 3.03 ng/mL and mean AUC0-24 was 21.3 ng•h/mL (Table 4). There is no accumulation of GM-CSF after repeat SC dosing and steady state conditions are met after a single SC dose.

Table 4: Sargramostim serum Cmax and AUC Exposure (CV%) in Humans after Subcutaneous Administration
Data type | Sargramostim dose | Formulation | Number of healthy subjects | AUC (CV%) (ng·h/mL) | Cmax(CV%) (ng/mL)
Observed | 6.5 mcg/kg | Lyophilized LEUKINE | 39 | 20.4 (28.7%) | 3.15 (35.2%)
Population PK model simulation | 7 mcg/kg | Lyophilized LEUKINE | 500 | 21.3 (32.6) | 3.03 (31.0)

Absorption

After SC administration GM-CSF was detected in the serum early (15 min) and reached maximum serum concentrations between 2.5 and 4 h. The absolute bioavailability with the SC route, when compared to the IV route, was 75%.

Distribution

The observed volume of distribution after IV (Vz) administration was 96.8.

Elimination

LEUKINE administered SC to healthy adult volunteers, GM-CSF had a terminal elimination half-life of 1.4 h. The observed total body clearance/subcutaneous bioavailability (CL/F) was 23 L/h. Specific metabolism studies were not conducted, because LEUKINE is a protein and is expected to degrade to small peptides and individual amino acids.

Special Populations

Adult patients acutely exposed to myelosuppressive doses of radiation (H-ARS)

The pharmacokinetics of sargramostim are not available in adult patients acutely exposed to myelosuppressive doses of radiation. Pharmacokinetic data in irradiated and non-irradiated non-human primates and in healthy human adults were used to derive human doses for patients acutely exposed to myelosuppressive doses of radiation. Modeling and simulation of the healthy human adult pharmacokinetic data indicate that sargramostim Cmax and AUC exposures at a LEUKINE dose of 7 mcg/kg in patients acutely exposed to myelosuppressive doses of radiation are expected to exceed sargramostim Cmax (97.6% of patients) and AUC (100% of patients) exposures at a LEUKINE dose of 7 mcg/kg in non-human primates.

Pediatric patients acutely exposed to myelosuppressive doses of radiation (H-ARS)

The pharmacokinetics of sargramostim was not available in pediatric patients acutely exposed to myelosuppressive doses of radiation. The pharmacokinetics of sargramostim in pediatric patients after being exposed to myelosuppressive doses of radiation were estimated by scaling the adult population pharmacokinetic model to the pediatric population. The model-predicted mean AUC0-24 values at 7, 10, and 12 mcg/kg doses of LEUKINE in pediatric patients weighing greater than 40 kg (~adolescents), 15 to 40 kg (~young children), and 0 to less than 15 kg (~newborns to toddlers), respectively, were similar to AUC values in adults after a 7 mcg/kg dose.

13 NONCLINICAL TOXICOLOGY

13.1 Carcinogenesis, Mutagenesis, Impairment of Fertility

Carcinogenesis and Mutagenesis

Carcinogenicity and genetic toxicology studies have not been conducted with LEUKINE.

Impairment of Fertility

LEUKINE had no effect on fertility of female rabbits up to a dose of 200 mcg/kg/day.

The toxicology studies with up to 6 weeks of exposure to LEUKINE in sexually mature female and male cynomolgus monkeys did not reveal findings in male or female reproductive organs that would suggest impairment of fertility up to a dose of 200 mcg/kg/day. At 200 mcg/kg, the AUC exposure of LEUKINE was 8.8 to 11.4 times (monkeys) and 2.0 to 25.3 times (rabbits) the exposure in humans at the recommended clinical dose of 250 mcg/m^2.

After the first administration, a dose of 200 mcg/kg/day corresponds to an AUC of approximately 11.4 (monkeys) and 25.3 (rabbits) times the exposures observed in patients treated with the clinical LEUKINE dose of 250 mcg/m^2; however, due to the production of anti-LEUKINE antibodies with repeat administration, the AUC decreased to 8.8 (monkeys) and 2.0 (rabbits) times the clinical exposure by the end of the dosing periods.

14 CLINICAL STUDIES

14.1 Following Induction Chemotherapy for Acute Myelogenous Leukemia

The efficacy of LEUKINE in the treatment of AML was evaluated in a multicenter, randomized, double-blind placebo-controlled trial (study 305) of 99 newly-diagnosed adult patients, 55-70 years of age, receiving induction with or without consolidation. A combination of standard doses of daunorubicin (days 1-3) and ara-C (days 1-7) was administered during induction and high dose ara-C was administered days 1-6 as a single course of consolidation, if given. Bone marrow evaluation was performed on day 10 following induction chemotherapy. If hypoplasia with <5% blasts was not achieved, patients immediately received a second cycle of induction chemotherapy. If the bone marrow was hypoplastic with <5% blasts on day 10 or four days following the second cycle of induction chemotherapy, LEUKINE (250 mcg/m^2/day) or placebo was given intravenously over four hours each day, starting four days after the completion of chemotherapy. Study drug was continued until an ANC ≥1500 cells/mm^3 for three consecutive days was attained or a maximum of 42 days. LEUKINE or placebo was also administered after the single course of consolidation chemotherapy if delivered (ara-C 3-6 weeks after induction following neutrophil recovery). Study drug was discontinued immediately if leukemic regrowth occurred.

LEUKINE significantly shortened the median duration of ANC <500 cells/mm3 by 4 days and <1000 cells/mm^3 by 7 days following induction (see Table 5). Of patients receiving LEUKINE, 75% achieved ANC >500 cells/mm^3 by day 16, compared to day 25 for patients receiving placebo. The proportion of patients receiving one cycle (70%) or two cycles (30%) of induction was similar in both treatment groups. LEUKINE significantly shortened the median times to neutrophil recovery whether one cycle (12 vs. 15 days) or two cycles (14 vs. 23 days) of induction chemotherapy was administered. Median times to platelet (>20,000 cells/mm^3) and RBC transfusion independence were not significantly different between treatment groups.

Table 5: Hematological Recovery (in Days) in Patients with AML: Induction
Dataset | LEUKINE n=52a Median (25%, 75%) | Placebo n=47 Median (25%, 75%) | p-valueb
ANC >500/mm3 c | 13 (11, 16) | 17 (13, 25) | 0.009
ANC >1000/mm3 d | 14 (12, 18) | 21 (13, 34) | 0.003
PLT >20,000/mm3 e | 11 (7, 14) | 12 (9, >42) | 0.10
RBCf | 12 (9, 24) | 14 (9, 42) | 0.53
a Patients with missing data censored
b p = Generalized Wilcoxon
c 2 patients on LEUKINE and 4 patients on placebo had missing values
d 2 patients on LEUKINE and 3 patients on placebo had missing values
e 4 patients on placebo had missing values
f 3 patients on LEUKINE and 4 patients on placebo had missing values

During the consolidation phase of treatment, LEUKINE did not shorten the median time to recovery of ANC to 500 cells/mm^3 (13 days) or 1000 cells/mm^3 (14.5 days) compared to placebo. There were no significant differences in time to platelet and RBC transfusion independence.

The incidence of severe infections and deaths associated with infections was significantly reduced in patients who received LEUKINE. During induction or consolidation, 27 of 52 patients receiving LEUKINE and 35 of 47 patients receiving placebo had at least one grade 3, 4 or 5 infection (p=0.02). Twenty-five patients receiving LEUKINE and 30 patients receiving placebo experienced severe and fatal infections during induction only. There were significantly fewer deaths from infectious causes in the LEUKINE arm (3 vs. 11, p=0.02). The majority of deaths in the placebo group were associated with fungal infections with pneumonia as the primary infection.

14.2 Autologous Peripheral Blood Progenitor Cell Mobilization and Collection

A retrospective review was conducted of data from adult patients with cancer undergoing collection of peripheral blood progenitor cells (PBPC) at a single transplant center. Mobilization of PBPC and myeloid reconstitution post transplant were compared between four groups of patients (n=196) receiving LEUKINE for mobilization and a historical control group who did not receive any mobilization treatment [progenitor cells collected by leukapheresis without mobilization (n=100)]. Sequential cohorts received LEUKINE. The cohorts differed by dose (125 or 250 mcg/m^2/day), route (IV over 24 hours or SC) and use of LEUKINE post transplant. Leukaphereses were initiated for all mobilization groups after the WBC reached 10,000 cells/mm^3. Leukaphereses continued until both a minimum number of mononucleated cells (MNC) were collected (6.5 or 8.0 × 10^8/kg body weight) and a minimum number of aphereses (5-8) were performed. Both minimum requirements varied by treatment cohort and planned conditioning regimen. If subjects failed to reach a WBC of 10,000 cells/mm^3 by day 5, another cytokine was substituted for LEUKINE.

Marked mobilization effects were seen in patients administered the higher dose of LEUKINE (250 mcg/m^2) either IV (n=63) or SC (n=41). PBPCs from patients treated at the 250 mcg/m^2/day dose had a significantly higher number of granulocyte-macrophage colony-forming units (CFU-GM) than those collected without mobilization. The mean value after thawing was 11.41 × 10^4 CFU-GM/kg for all LEUKINE-mobilized patients, compared to 0.96 × 10^4/kg for the non-mobilized group. A similar difference was observed in the mean number of erythrocyte burst-forming units (BFU-E) collected (23.96 × 10^4/kg for patients mobilized with 250 mcg/m^2 doses of LEUKINE administered SC vs. 1.63 × 10^4/kg for non-mobilized patients).

A second retrospective review of data from patients undergoing PBPC at another single transplant center was also conducted. LEUKINE was given SC at 250 mcg/m^2/day once a day (n=10) or twice a day (n=21) until completion of apheresis. Apheresis was begun on day 5 of LEUKINE administration and continued until the targeted MNC count of 9 × 10^8/kg or CD34+ cell count of 1 × 10^6/kg was reached. There was no difference in CD34+ cell count in patients receiving LEUKINE once or twice a day.

14.3 Autologous Peripheral Blood Progenitor Cell and Bone Marrow Transplantation

The efficacy of LEUKINE to accelerate myeloid reconstitution following autologous PBPC was established in the retrospective review above. After transplantation, mobilized subjects had shorter times to neutrophil recovery and fewer days between transplantation and the last platelet transfusion compared to non-mobilized subjects. Neutrophil recovery (ANC >500 cells/mm^3) was more rapid in patients administered LEUKINE following PBPC transplantation with LEUKINE-mobilized cells (see Table 6). Mobilized patients also had fewer days to the last platelet transfusion and last RBC transfusion, and a shorter duration of hospitalization than did non-mobilized subjects.

Table 6: ANC and Platelet Recovery after PBPC Transplantation
 | LEUKINE Route for Mobilization | Post transplant LEUKINE | Median Day ANC >500 cells/mm^3 | Median Day of Last platelet transfusion
No Mobilization | — | No | 29 | 28
LEUKINE 250 mcg/m^2 | IV | No | 21 | 24
LEUKINE 250 mcg/m^2 | IV | Yes | 12 | 19
LEUKINE 250 mcg/m^2 | SC | Yes | 12 | 17

The efficacy of LEUKINE on time to myeloid reconstitution following autologous BMT was established by three single-center, randomized, placebo-controlled and double-blinded studies (studies 301, 302, and 303) in adult and pediatric patients undergoing autologous BMT for lymphoid malignancies. A total of 128 patients (65 LEUKINE, 63 placebo) were enrolled in these three studies. The median age was 38 years (range 3-62 years), and 12 patients were younger than 18 years of age. The majority of the patients had lymphoid malignancy (87 NHL, 17 ALL), 23 patients had Hodgkin lymphoma, and one patient had AML. In 72 patients with NHL or ALL, the bone marrow harvest was purged with one of several monoclonal antibodies prior to storage. No chemical agent was used for in vitro treatment of the bone marrow. Preparative regimens in the three studies included cyclophosphamide (total dose 120-150 mg/kg) and total body irradiation (total dose 1,200-1,575 rads). Other regimens used in patients with Hodgkin's disease and NHL without radiotherapy consisted of three or more of the following in combination (expressed as total dose): cytosine arabinoside (400 mg/m^2) and carmustine (300 mg/m^2), cyclophosphamide (140-150 mg/kg), hydroxyurea (4.5 grams/m^2), and etoposide (375-450 mg/m^2).

Compared to placebo, administration of LEUKINE in two studies (study 301: 44 patients, 23 patients treated with LEUKINE, and study 303: 47 patients, 24 treated with LEUKINE) significantly improved the following hematologic and clinical endpoints: time to neutrophil recovery, duration of hospitalization and infection experience or antibacterial usage. In the third study (study 302: 37 patients who underwent autologous BMT, 18 treated with LEUKINE) there was a positive trend toward earlier myeloid engraftment in favor of LEUKINE. This latter study differed from the other two in having enrolled a large number of patients with Hodgkin lymphoma who had also received extensive radiation and chemotherapy prior to harvest of autologous bone marrow. In the following combined analysis of the three studies, these two subgroups (NHL and ALL vs. Hodgkin lymphoma) are presented separately.

Patients with Lymphoid Malignancy (Non-Hodgkin's Lymphoma and Acute Lymphoblastic Leukemia)

Neutrophil recovery (ANC ≥500 cells/mm^3) in 54 patients with NHL or ALL receiving LEUKINE on Studies 301, 302 and 303 was observed on day 18, and on day 24 in 50 patients treated with placebo (see Table 7). The median duration of hospitalization was six days shorter for the LEUKINE group than for the placebo group. Median duration of infectious episodes (defined as fever and neutropenia; or two positive cultures of the same organism; or fever >38°C and one positive blood culture; or clinical evidence of infection) was three days less in the group treated with LEUKINE. The median duration of antibacterial administration in the post transplantation period was four days shorter for the patients treated with LEUKINE than for placebo-treated patients.

Table 7: Autologous BMT: Combined Analysis from Placebo-Controlled Clinical Trials of Responses in Patients with NHL and ALL Median Values (days)
 | ANC ≥500 cells /mm^3 | ANC ≥1000 cells /mm^3 | Duration of Hospitalization | Duration of Infection | Duration of Antibacterial Therapy
LEUKINE n=54 | 18a, b | 24a, b | 25a | 1a | 21a
Placebo n=50 | 24 | 32 | 31 | 4 | 25
a p <0.05 Wilcoxon or Cochran-Mantel-Haenszel RIDIT chi-squared
b p <0.05 Log rank

14.4 Allogeneic Bone Marrow Transplantation

A multicenter, randomized, placebo-controlled, and double-blinded study (study 9002) was conducted to evaluate the safety and efficacy of LEUKINE for promoting hematopoietic reconstitution following allogeneic BMT. A total of 109 adult and pediatric patients (53 LEUKINE, 56 placebo) were enrolled in the study. The median age was 34.7 years (range 2.2-65.1 years). Twenty-three patients (11 LEUKINE, 12 placebo) were 18 years old or younger. Sixty-seven patients had myeloid malignancies (33 AML, 34 CML), 17 had lymphoid malignancies (12 ALL, 5 NHL), three patients had Hodgkin's disease, six had multiple myeloma, nine had myelodysplastic disease, and seven patients had aplastic anemia. In 22 patients at one of the seven study sites, bone marrow harvests were depleted of T cells. Preparative regimens included cyclophosphamide, busulfan, cytosine arabinoside, etoposide, methotrexate, corticosteroids, and asparaginase. Some patients also received total body, splenic, or testicular irradiation. Primary GVHD prophylaxis was cyclosporine and a corticosteroid.

Accelerated myeloid engraftment was associated with significant laboratory and clinical benefits. Compared to placebo, administration of LEUKINE significantly improved the following: time to neutrophil engraftment, duration of hospitalization, number of patients with bacteremia, and overall incidence of infection (see Table 8).

Table 8: Allogeneic BMT: Analysis of Data from Placebo-Controlled Clinical Trial Median Values (days or number of patients)
 | ANC ≥500 cells /mm^3 | ANC ≥1000 cells /mm^3 | Number of Patients with Infections | Number of Patients with Bacteremia | Days of Hospitalization
LEUKINE n=53 | 13a | 14a | 30a | 9b | 25a
Placebo n=56 | 17 | 19 | 42 | 19 | 26
a p <0.05 generalized Wilcoxon test
b p <0.05 simple chi-square test

Median time to myeloid recovery (ANC ≥500 cells/mm^3) in 53 patients receiving LEUKINE was 4 four days less than in 56 patients treated with placebo (see Table 8). The numbers of patients with bacteremia and infection were significantly lower in the LEUKINE group compared to the placebo group (9/53 versus 19/56 and 30/53 versus 42/56, respectively). There were a number of secondary laboratory and clinical endpoints. Of these, only the incidence of severe (grade 3/4) mucositis was significantly improved in the LEUKINE group (4/53) compared to the placebo group (16/56) at p<0.05. LEUKINE-treated patients also had a shorter median duration of post transplant IV antibiotic infusions, and a shorter median number of days to last platelet and RBC transfusions compared to placebo patients, but none of these differences reached statistical significance.

14.5 Treatment of Delayed Neutrophil Recovery or Graft Failure After Allogeneic or Autologous Bone Marrow Transplantation

A historically-controlled study (study 501) was conducted in patients experiencing graft failure following allogeneic or autologous BMT to determine whether LEUKINE improved survival after BMT failure.

Three categories of patients were eligible for this study:

1. patients displaying a delay in neutrophil recovery (ANC ≤100 cells/mm^3 by day 28 post transplantation);
2. patients displaying a delay in neutrophil recovery (ANC ≤100 cells/mm^3 by day 21 post transplantation) and who had evidence of an active infection; and
3. patients who lost their marrow graft after a transient neutrophil recovery (manifested by an average of ANC ≥500 cells/mm^3 for at least one week followed by loss of engraftment with ANC <500 cells/mm^3 for at least one week beyond day 21 post transplantation).

A total of 140 eligible adult and pediatric patients from 35 institutions were treated with LEUKINE and evaluated in comparison to 103 historical control patients from a single institution. One hundred sixty-three patients had lymphoid or myeloid leukemia, 24 patients had NHL, 19 patients had Hodgkin's disease and 37 patients had other diseases, such as aplastic anemia, myelodysplasia or non-hematologic malignancy. The majority of patients (223 out of 243) had received prior chemotherapy with or without radiotherapy and/or immunotherapy prior to preparation for transplantation. The median age of enrolled patients was 27 years (range 1-66 years). Thirty-seven patients were younger than 18 years of age.

One hundred-day survival was improved in favor of the patients treated with LEUKINE for graft failure following either autologous or allogeneic BMT. In addition, the median survival was improved by greater than two-fold. The median survival of patients treated with LEUKINE after autologous failure was 474 days versus 161 days for the historical patients. Similarly, after allogeneic failure, the median survival was 97 days with LEUKINE treatment and 35 days for the historical controls. Improvement in survival was better in patients with fewer impaired organs. The Multiple Organ Failure (MOF) score is a clinical and laboratory assessment of seven major organ systems: cardiovascular, respiratory, gastrointestinal, hematologic, renal, hepatic, and neurologic. Median survival by MOF category is presented in Table 9.

Table 9: Median Survival by Multiple Organ Failure (MOF) Category Median Survival (days)
 | MOF ≤2 Organs | MOF >2 Organs | MOF (Composite of both groups)
Autologous BMT
LEUKINE | 474 (n=58) | 78.5 (n=10) | 474 (n=68)
Historical | 165 (n=14) | 39 (n=3) | 161 (n=17)
Allogeneic BMT
LEUKINE | 174 (n=50) | 27 (n=22) | 97 (n=72)
Historical | 52.5 (n=60) | 15.5 (n=26) | 35 (n=86)

14.6 Acute Exposure to Myelosuppressive Doses of Radiation (H-ARS)

Efficacy studies of LEUKINE could not be conducted in humans with acute radiation syndrome for ethical and feasibility reasons. The use of LEUKINE in the H-ARS indication was based on efficacy studies conducted in animals and data supporting LEUKINE’s effect on severe neutropenia in patients undergoing autologous or allogeneic BMT following myelosuppressive chemotherapy with or without total body irradiation, and in patients with acute myelogenous leukemia following myelosuppressive chemotherapy [see Dosage and Administration (2.1 to 2.6)].

The recommended dose of LEUKINE for adults exposed to myelosuppressive doses of radiation is 7 mcg/kg as a single daily SC injection [see Dosage and Administration (2.6)]. The 7 mcg/kg dosing regimen is based on population modeling and simulation analyses. The sargramostim exposure associated with the 7 mcg/kg adult dose is expected to be higher than sargramostim exposure in the nonclinical efficacy study and therefore are expected to provide sufficient pharmacodynamic activity to treat humans exposed to myelosuppressive doses of radiation [see Clinical Pharmacology (12.3)]. The safety of LEUKINE at a dose of 250 mcg/m^2/day (approximately 7 mcg/kg) has been assessed on the basis of clinical experience in myeloid reconstitution in patients after autologous or allogeneic BMT, and in patients with AML [see Adverse Reactions (6.1)].

The efficacy of LEUKINE was studied in a randomized, blinded, placebo-controlled study in a nonhuman primate model of radiation injury. Rhesus macaques (50% male) were randomized to a control (n = 36) or treated (n = 36) group. Animals were exposed to total body irradiation at a dose that would be lethal in 50% to 60% of animals (655 cGy) by day 60 post irradiation (lethal dose [LD]50-60/60). Starting 48 ± 1 hour after irradiation, animals received daily SC injections of placebo (sterile water for injection, USP) or LEUKINE (7 mcg/kg/day). Blinded treatment was stopped when one of the following criteria was met: ANC ≥1,000 cells/mm^3 for 3 consecutive days or if the ANC ≥10,000 cells/mm^3. Animals received minimal supportive care that included a prophylactic antibiotic, antiemetic, analgesics, and parenteral fluids. No whole blood, blood products or individualized antibiotics were provided.

LEUKINE significantly (p=0.0018) increased survival at day 60 in irradiated nonhuman primates: 78% survival (28/36) in the LEUKINE group compared to 42% survival (15/36) in the control group.

In the same study, an exploratory cohort of 36 rhesus macaques randomized to control (n=18) or treated (n=18) was exposed to total body irradiation at a dose that would be lethal in 70-80% of animals (713 cGY) by day 60 post irradiation. LEUKINE increased survival at day 60 in irradiated nonhuman primates: 61% survival (11/18) in the LEUKINE group compared to 17% survival (3/18) in the control group.

16 HOW SUPPLIED/STORAGE AND HANDLING

How Supplied

LEUKINE (sargramostim) for injection is a sterile, preservative-free, white lyophilized powder supplied in a carton containing five 250 mcg single-dose vials. (NDC 71837-5843-5).

Storage and Handling

Store LEUKINE vials refrigerated at 2°C to 8°C (36°F to 46°F) in the original carton to protect from light. Do not freeze or shake. Do not use beyond the expiration date printed on the vial.

17 PATIENT COUNSELING INFORMATION

Advise the patient to read the FDA-approved patient labeling (Patient Information).

LEUKINE should be used under the guidance and supervision of a health care professional. However, if the physician determines that LEUKINE may be used outside of the hospital or office setting, persons who will be administering LEUKINE should be instructed as to the proper dose, and the method of reconstituting and administering LEUKINE [see Dosage and Administration (2.7)]. If home use is prescribed, patients should be instructed in the importance of proper disposal and cautioned against the reuse of needles, syringes, drug product, and diluent. A puncture resistant container should be used by the patient for the disposal of used needles.

Advise patients of the following risks and potential risks with LEUKINE:

- Serious allergic reactions [see Warnings and Precautions (5.1)]
- Infusion related reactions [see Warnings and Precautions (5.2)]
- Risk of severe myelosuppression when LEUKINE administered within 24 hours of chemotherapy or radiotherapy [see Warnings and Precautions (5.3)]
- Effusions and capillary leak syndrome [see Warnings and Precautions (5.4)]
- Supraventricular arrhythmias [see Warnings and Precautions (5.5)]
- Leukocytosis including eosinophilia [see Warnings and Precautions (5.6)]
- Potential effect on malignant cells [see Warnings and Precautions (5.7)]
- Pain including chest, abdominal, back, and joint pain [see Adverse Reactions (6.1)]
- Thromboembolic events [see Adverse Reactions (6.3)]
- Embryofetal Toxicity: Advise females of reproductive potential that LEUKINE may cause fetal harm and to inform their prescriber of a known or suspected pregnancy [see Use in Specific Populations (8.1)]
- Lactation: Advise lactating woman not to breastfeed during treatment and for at least 2 weeks after the last dose [see Use in Specific Populations (8.2)]
- Advise patients acutely exposed to myelosuppressive doses of radiation (H-ARS) that efficacy studies of LEUKINE for this indication could not be conducted in humans for ethical and feasibility reasons and that, therefore, approval of this use was based on efficacy studies conducted in animals [see Clinical Studies (14.6)]

Instruct patients who self-administer LEUKINE:

- Do not reuse needles, syringes, or unused portions of vials
- Follow local requirements for proper disposal of used syringes, needles, and unused vials

LEUKINE® is a registered trademark licensed to Partner Therapeutics, Inc. Partner Therapeutics is a registered trademark of Partner Therapeutics, Inc.
Manufactured by: Partner Therapeutics, Inc., Lexington, MA 02421
US License No. 2087
©2023 Partner Therapeutics, Inc. All rights reserved.

(VER-AW009-02) Phone: 1-888-4RX-LEUKINE

Patient Information

LEUKINE® (loo-kine)
(sargramostim)
injection

LEUKINE® (loo-kine)
(sargramostim)
for injection

What is LEUKINE?

LEUKINE is a man-made form of granulocyte-macrophage colony-stimulating factor (GM-CSF). GM-CSF is a substance produced by the body. It stimulates the growth of certain white blood cells that are important in the body’s fight against infection.

Acute Radiation Syndrome: The effectiveness of LEUKINE for this use was only studied in animals because it could not be studied in people.

Do not take LEUKINE if you have had a serious allergic reaction to human GM-CSF, such as sargramostim, products that are made from yeast, or any of the ingredients in LEUKINE. See the end of this leaflet for a complete list of ingredients in LEUKINE.

Before receiving LEUKINE, tell your healthcare provider about all your medical conditions, including if you:

- have heart or lung disease
- are allergic to benzyl alcohol
- are pregnant or plan to become pregnant. It is not known if LEUKINE will harm your unborn baby. See “What are the possible side effects of LEUKINE?” Talk to your healthcare provider about the type of LEUKINE that is right for you.
- are breastfeeding or plan to breastfeed. It is not known if LEUKINE passes into your breast milk. Do not breast feed during treatment and for at least 2 weeks after your last dose of LEUKINE.

Tell your healthcare provider about all the medicines you take, including prescription and over-the-counter medicines, vitamins, and herbal supplements.

How will I receive LEUKINE?

- LEUKINE comes in two ways: as a solution or as a powder to be mixed for injection.
- LEUKINE is given as an injection under your skin (subcutaneous injection) by a healthcare provider.
- If your healthcare provider decides that the subcutaneous injections can be given at home by you or your caregiver, see the detailed “Instructions for Use” that comes with your LEUKINE for information on how to draw up and inject a dose of LEUKINE.
- If your healthcare provider gives you LEUKINE for injection (powder) to be mixed, carefully follow your healthcare provider’s instructions on how to store, mix, draw up and inject the medicine.
- You and your caregiver should be shown how to prepare and inject LEUKINE before you use it, by your healthcare provider.
- Your healthcare provider will tell you how much LEUKINE to inject and when to inject it. Do not change your dose or stop LEUKINE unless your healthcare provider tells you to.
- If you are also receiving chemotherapy or radiation therapy, your dose of LEUKINE should be injected at least 24 hours before or 24 hours after your dose of chemotherapy and at least 24 hours before your dose of radiation therapy. Your healthcare provider will do blood tests to monitor your white blood cell count and, if necessary, adjust your LEUKINE dose.
- If you are receiving LEUKINE because you have been suddenly (acutely) exposed to an amount of radiation that can affect your bone marrow (Acute Radiation Syndrome), you will need to have blood tests about every 3 days during treatment with LEUKINE to check your white blood cell count until it returns to normal.
- If your child needs to receive LEUKINE for Acute Radiation Syndrome, follow your healthcare provider’s instructions. LEUKINE injection contains the preservative benzyl alcohol.
- If you miss a dose of LEUKINE, talk to your healthcare provider about when you should give your next dose.

What are the possible side effects of LEUKINE?

LEUKINE may cause serious side effects, including:

- Serious allergic reactions. LEUKINE can cause serious allergic reactions that can be severe. Get medical help right away if you get any of the following signs or symptoms of a serious allergic reaction with LEUKINE, including: skin rash over your entire body, hives, trouble breathing, wheezing, swelling around your mouth or eyes, a fast heartbeat, sweating, and dizziness or feeling faint.
- Infusion related reactions. When LEUKINE is given as an infusion, it can cause reactions during or soon after an infusion. Tell your healthcare provider or nurse right away if you develop trouble breathing, skin flushing, a fast pulse, dizziness or you feel faint during or soon after your infusion.
- Too much body fluid (fluid retention) and Capillary Leak Syndrome. LEUKINE can cause you to have too much fluid in your body, and fluid may leak from blood vessels into your body’s tissues. This can happen anywhere in your body, including around your heart and lungs. This condition is called “Capillary Leak Syndrome” (CLS). CLS can quickly cause you to have symptoms that may become life-threatening. Get emergency medical help right away if you develop any of the following symptoms:
  - swelling or puffiness of your feet or ankles, and are urinating less than usual
  - swelling of your stomach area (abdomen) and feeling of fullness
  - sudden weight gain
  - swollen legs or feet
  - trouble breathing
  - dizziness or feeling faint
  - a general feeling of tiredness
- Abnormal heart rhythm. An abnormal heart rhythm may happen during treatment with LEUKINE, especially in people with a history of an abnormal heart rhythm.
- Increased white blood cell count. LEUKINE can cause your white blood cell count to increase too high (leukocytosis). Your healthcare provider will check your blood during treatment with LEUKINE.
- Risks of using LEUKINE in newborns, babies born with a low birth weight, and in pregnant women. Some forms of LEUKINE may contain the preservative benzyl alcohol. Medicines that contain benzyl alcohol, including LEUKINE, can cause serious side effects that can lead to death in newborns and babies born with a low birth weight. Avoid using LEUKINE containing benzyl alcohol in newborns, babies born with a low birth weight, and in pregnant women. If LEUKINE needs to be given to your newborn or baby with a low birth weight, or in pregnant women, talk to your healthcare provider about this risk and which form of LEUKINE to use.

The most common side effects of LEUKINE in people who receive an autologous bone marrow transplant include: fever, nausea, diarrhea, vomiting, mouth sores, weakness and lack of energy, generally do not feel well, decreased appetite, rash, stomach and intestine problems, fluid buildup.

The most common side effects of LEUKINE in people who receive an allogeneic bone marrow transplant include: diarrhea, fever, nausea, rash, vomiting, mouth sores, decreased appetite, hair loss, stomach-area (abdomen) pain, headache and high blood pressure.

The most common side effects of LEUKINE LEUKINE in people with AML include: fever, liver problems, skin reactions, infections, abnormal amount of salts and other minerals in the blood, nausea, diarrhea, urinary tract problems, lung problems, vomiting, nervous system problems, mouth sores, hair loss and weight loss.

These are not all the possible side effects of LEUKINE.
Call your healthcare provider for medical advice about side effects. You may report side effects to FDA at 1-800-FDA-1088.

How should I store LEUKINE injection (solution)?

- Store LEUKINE in the refrigerator between 36°F to 46°F (2°C to 8°C).
- Do not freeze LEUKINE.
- Do not shake.
- Store LEUKINE vials in the original carton to protect from light.
- Do not use LEUKINE beyond the expiration date printed on the vial label.
- Used vials with remaining LEUKINE should be stored in the refrigerator and used within 20 days (be sure to mark down the date you first used the vial).
- Throw away (dispose of) any remaining LEUKINE after 20 days.

Keep LEUKINE out of the reach of children.

General information about the safe and effective use of LEUKINE.

Medicines are sometimes prescribed for purposes other than those listed in a Patient Information leaflet. Do not use LEUKINE for a condition for which it was not prescribed. Do not give LEUKINE to other people, even if they have the same symptoms that you have. It may harm them. You can ask your pharmacist or healthcare provider for information about LEUKINE that is written for health professionals.

What are the ingredients in LEUKINE?

Active ingredient: sargramostim

Inactive ingredients:
LEUKINE injection: benzyl alcohol
LEUKINE for injection: mannitol, sucrose, tromethamine

LEUKINE® is a registered trademark licensed to Partner Therapeutics, Inc.
Manufactured by: Partner Therapeutics, Inc., Lexington, MA 02421
US License No. 2087
©2018 Partner Therapeutics, Inc.
For more information go to www.leukine.com, or call 1-888-4RX-LEUKINE

This Patient Information has been approved by the U.S. Food and Drug Administration

Revised: 05/2018